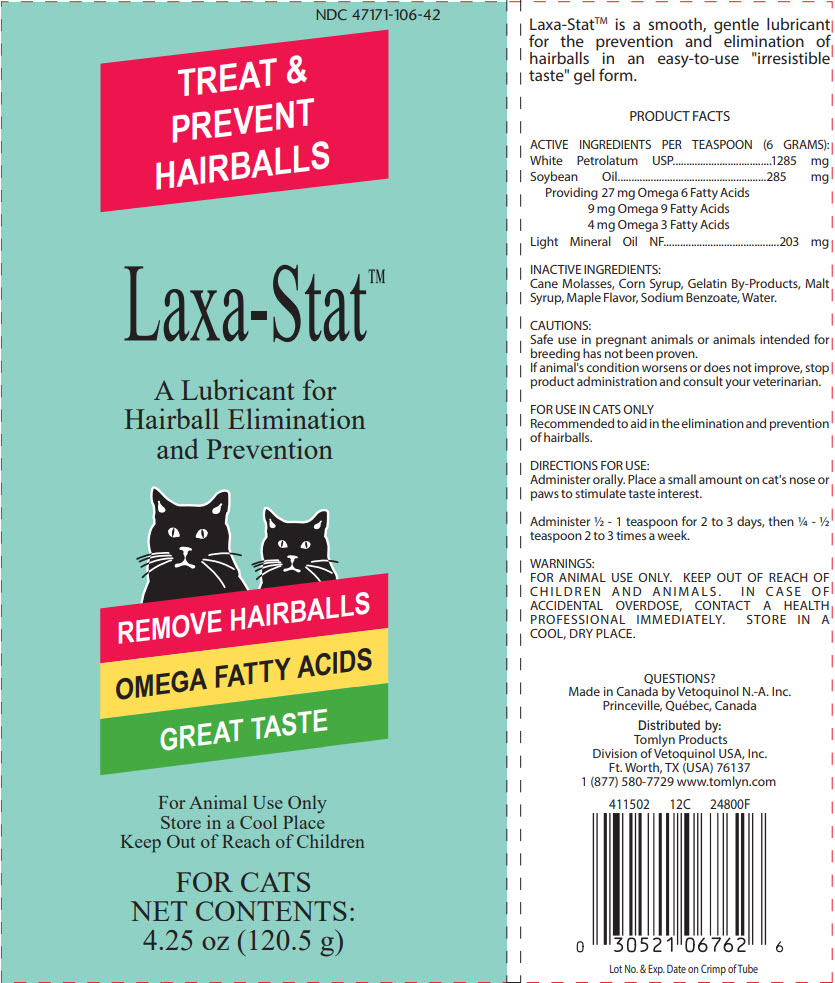 DRUG LABEL: Laxa-Stat
NDC: 47171-019 | Form: GEL
Manufacturer: Tomlyn Products, a Divison of Vetoquinil USA, Inc.
Category: animal | Type: OTC ANIMAL DRUG LABEL
Date: 20181002

ACTIVE INGREDIENTS: Petrolatum 214.2 mg/1 g; Mineral Oil 33.8 mg/1 g; Soybean Oil 47.5 mg/1 g
INACTIVE INGREDIENTS: Corn Syrup; Maltose Syrup; Molasses; Gelatin, Unspecified; Sodium Benzoate; Water

Laxa-Stat™

VETERINARY INDICATIONS

Laxa-Stat™ is a smooth, gentle lubricant for the prevention and elimination of hairballs in an easy-to-use "irresistible taste" gel form.

PRODUCT FACTS

DESCRIPTION

ACTIVE INGREDIENTS PER TEASPOON (6 GRAMS):

White Petrolatum USP | 1285 mg
Soybean Oil | 285 mg
Providing 27 mg Omega 6 Fatty Acids 9 mg Omega 9 Fatty Acids 4 mg Omega 3 Fatty Acids
Light Mineral Oil NF | 203 mg

INACTIVE INGREDIENTS:

Cane Molasses, Corn Syrup, Gelatin By-Products, Malt Syrup, Maple Flavor, Sodium Benzoate, Water.

SAFE HANDLING WARNING

CAUTIONS:

Safe use in pregnant animals or animals intended for breeding has not been proven.

If animal's condition worsens or does not improve, stop product administration and consult your veterinarian.

FOR USE IN CATS ONLY

Recommended to aid in the elimination and prevention of hairballs.

DOSAGE AND ADMINISTRATION

DIRECTIONS FOR USE:

Administer orally. Place a small amount on cat's nose or paws to stimulate taste interest.

Administer ½ - 1 teaspoon for 2 to 3 days, then ¼ - ½ teaspoon 2 to 3 times a week.

WARNINGS:

FOR ANIMAL USE ONLY. KEEP OUT OF REACH OF CHILDREN AND ANIMALS. IN CASE OF ACCIDENTAL OVERDOSE, CONTACT A HEALTH PROFESSIONAL IMMEDIATELY. STORE IN A COOL, DRY PLACE.

QUESTIONS?

Made in Canada by Vetoquinol N.-A. Inc.
Princeville, Québec, Canada

Distributed by:
Tomlyn Products
Division of Vetoquinol USA, Inc.
Ft. Worth, TX (USA) 76137
1 (877) 580-7729 www.tomlyn.com

411502
12C
24800F

Lot No. & Exp. Date on Crimp of Tube

PRINCIPAL DISPLAY PANEL - 120.5 g Tube Label

NDC 47171-106-42

TREAT &
PREVENT
HAIRBALLS

Laxa-Stat™

A Lubricant for
Hairball Elimination
and Prevention

REMOVE HAIRBALLS
OMEGA FATTY ACIDS
GREAT TASTE

For Animal Use Only
Store in a Cool Place
Keep Out of Reach of Children

FOR CATS
NET CONTENTS:
4.25 oz (120.5 g)